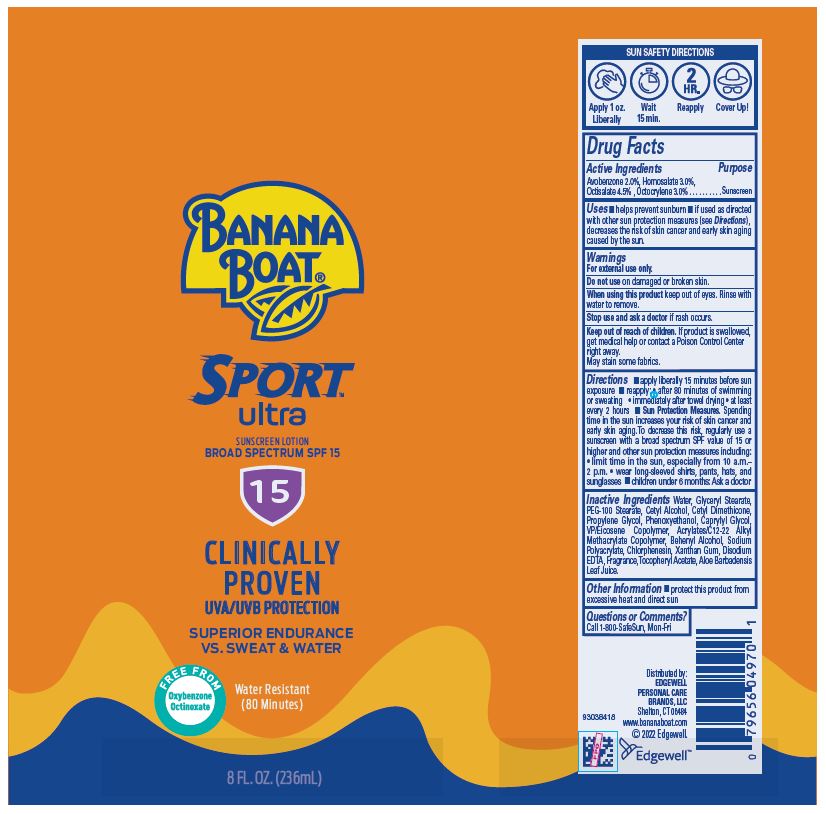 DRUG LABEL: Banana Boat Ultra Sport Sunscreen Broad Spectrum SPF 15
NDC: 63354-204 | Form: LOTION
Manufacturer: Edgewell Personal Care Brands, LLC
Category: otc | Type: HUMAN OTC DRUG LABEL
Date: 20241027

ACTIVE INGREDIENTS: AVOBENZONE 2 g/100 g; OCTISALATE 4.5 g/100 g; OCTOCRYLENE 3 g/100 g; HOMOSALATE 3 g/100 g
INACTIVE INGREDIENTS: GLYCERYL 1-STEARATE; CETYL ALCOHOL; ALPHA-TOCOPHEROL ACETATE; CETYL DIMETHICONE 150; VINYLPYRROLIDONE/EICOSENE COPOLYMER; CHLORPHENESIN; XANTHAN GUM; DOCOSANOL; EDETATE DISODIUM ANHYDROUS; SODIUM POLYACRYLATE (2500000 MW); ALOE VERA LEAF; PROPYLENE GLYCOL; PHENOXYETHANOL; CAPRYLYL GLYCOL; WATER; POLYOXYL 100 STEARATE

Active Ingredients

Avobenzone 2.0%, Homosalate 3.0%, Octisalate 4.5%, Octocrylene 3.0%

Purpose

Sunscreen

Uses

• helps prevent sunburn • if used as directed with other sun protection measures (see Directions), decreases the risk of skin cancer and early skin aging caused by the sun

Warnings

For external use only

May stain some fabrics.

Do not use

on damaged or broken skin

When using this product

keep out of eyes. Rinse with water to remove.

Stop use and ask a doctor

if rash occurs.

Keep out of reach of children.

If product is swallowed, get medical help or contact a Poison Control Center right away.

Directions

• apply liberally 15 minutes before sun exposure • reapply: • after 80 minutes of swimming or sweating • immediately after towel drying • at least every 2 hours • Sun Protection Measures. Spending time in the sun increases your risk of skin cancer and early skin aging. To decrease this risk, regularly use a sunscreen with a broad spectrum SPF of 15 or higher and other sun protection measures including: • limit time in the sun, especially from 10 a.m. - 2 p.m. • wear long-sleeved shirts, pants, hats, and sunglasses • children under 6 months: Ask a doctor

Inactive ingredients

Water, Glyceryl Stearate, PEG-100 Stearate, Cetyl Alcohol, Cetyl Dimethicone, Propylene Glycol, Phenoxyethanol, Caprylyl Glycol, VP/Eicosene Copolymer, Acrylates/C12-22 Alkyl Methacrylate Copolymer, Behenyl Alcohol, Sodium Polyacrylate, Chlorphenesin, Xanthan Gum, Disodium EDTA, Fragrance, Tocopheryl Acetate, Aloe Barbadensis Leaf Juice

Other information

• protect this product from excessive heat and direct sun

Questions or Comments?

Call 1-800-SafeSun, Mon-Fri

Principal Display Panel

BANANA BOAT®
SPORT
Ultra
SUNSCREEN LOTION
BROAD SPECTRUM SPF 15
CLINICALLY
PROVEN
UVA/UVB PROTECTION
SUPERIOR ENDURANCE
VS. SWEAT & WATER
FREE FROM
Oxybenzone
Octinozate
Water Resistant
(80 Minutes)
8 FL. OZ. (236mL)